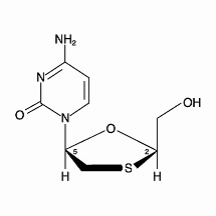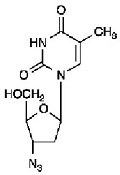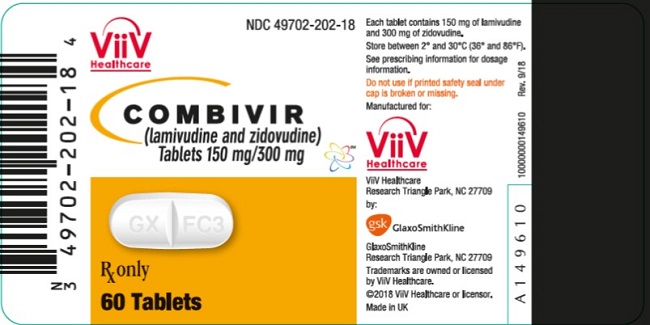 DRUG LABEL: COMBIVIR
NDC: 49702-202 | Form: TABLET, FILM COATED
Manufacturer: ViiV Healthcare Company
Category: prescription | Type: HUMAN PRESCRIPTION DRUG LABEL
Date: 20230822

ACTIVE INGREDIENTS: LAMIVUDINE 150 mg/1 1; ZIDOVUDINE 300 mg/1 1
INACTIVE INGREDIENTS: SILICON DIOXIDE; HYPROMELLOSE, UNSPECIFIED; MAGNESIUM STEARATE; MICROCRYSTALLINE CELLULOSE; POLYETHYLENE GLYCOL, UNSPECIFIED; POLYSORBATE 80; SODIUM STARCH GLYCOLATE TYPE A POTATO; TITANIUM DIOXIDE

HIGHLIGHTS OF PRESCRIBING INFORMATION

These highlights do not include all the information needed to use COMBIVIR safely and effectively. See full prescribing information for COMBIVIR.
COMBIVIR (lamivudine and zidovudine tablets), for oral use
Initial U.S. Approval: 1997

WARNING: HEMATOLOGIC TOXICITY, MYOPATHY, LACTIC ACIDOSIS AND SEVERE HEPATOMEGALY WITH STEATOSIS, and EXACERBATIONS OF HEPATITIS B

See full prescribing information for complete boxed warning

- Hematologic toxicity, including neutropenia and anemia, has been associated with the use of zidovudine, a component of COMBIVIR. (5.1)
- Symptomatic myopathy associated with prolonged use of zidovudine. (5.2)
- Lactic acidosis and severe hepatomegaly with steatosis, including fatal cases, have been reported with the use of nucleoside analogues including lamivudine and zidovudine (components of COMBIVIR). Suspend treatment if clinical or laboratory findings suggestive of lactic acidosis or pronounced hepatotoxicity occur. (5.3)
- Severe acute exacerbations of hepatitis B have been reported in patients who are co-infected with hepatitis B virus (HBV) and human immunodeficiency virus (HIV‑1) and have discontinued lamivudine, a component of COMBIVIR. Monitor hepatic function closely in these patients and, if appropriate, initiate anti-hepatitis B treatment. (5.4)

1 INDICATIONS AND USAGE

COMBIVIR, a combination of 2 nucleoside analogue reverse transcriptase inhibitors, is indicated in combination with other antiretroviral agents for the treatment of HIV‑1 infection. (1)

2 DOSAGE AND ADMINISTRATION

- Adults and Adolescents weighing greater than or equal to 30 kg: 1 tablet orally twice daily. (2.1)
- Pediatrics weighing greater than or equal to 30 kg: 1 tablet orally twice daily. (2.2)
- Because COMBIVIR is a fixed‑dose tablet and cannot be dose adjusted, COMBIVIR is not recommended in patients requiring dosage adjustment or with hepatic impairment or experiencing dose‑limiting adverse reactions. (2.3, 4)

3 DOSAGE FORMS AND STRENGTHS

Tablets: Scored 150 mg lamivudine and 300 mg zidovudine (3)

4 CONTRAINDICATIONS

COMBIVIR is contraindicated in patients with a previous hypersensitivity reaction to lamivudine or zidovudine. (4)

5 WARNINGS AND PRECAUTIONS

- Hepatic decompensation, some fatal, has occurred in HIV‑1/HCV co‑infected patients receiving combination antiretroviral therapy and interferon alfa with/without ribavirin. Discontinue COMBIVIR as medically appropriate and consider dose reduction or discontinuation of interferon alfa, ribavirin, or both. (5.5)
- Exacerbation of anemia has been reported in HIV‑1/HCV co‑infected patients receiving ribavirin and zidovudine. Coadministration of ribavirin and zidovudine is not advised. (5.5)
- Pancreatitis: Use with caution in patients with a history of pancreatitis or other significant risk factors for pancreatitis. Discontinue treatment as clinically appropriate. (5.6)
- Immune reconstitution syndrome and lipoatrophy have been reported in patients treated with combination antiretroviral therapy. (5.7, 5.8)

6 ADVERSE REACTIONS

- Most commonly reported adverse reactions (incidence greater than or equal to 15%) in clinical trials of combination lamivudine and zidovudine were headache, nausea, malaise and fatigue, nasal signs and symptoms, diarrhea, and cough. (6.1)

To report SUSPECTED ADVERSE REACTIONS, contact ViiV Healthcare at 1-877-844-8872 or FDA at 1-800-FDA-1088 or www.fda.gov/medwatch.

7 DRUG INTERACTIONS

- Agents antagonistic with zidovudine: Concomitant use should be avoided. (7.1)
- Hematologic/bone marrow suppressive/cytotoxic agents: May increase the hematologic toxicity of zidovudine. (7.1)
- Sorbitol: Coadministration of lamivudine and sorbitol may decrease lamivudine concentrations; when possible, avoid chronic coadministration. (7.2)

8 USE IN SPECIFIC POPULATIONS

- Lactation: Women infected with HIV should be instructed not to breastfeed due to the potential for HIV transmission. (8.2)

FULL PRESCRIBING INFORMATION

WARNING: HEMATOLOGIC TOXICITY, MYOPATHY, LACTIC ACIDOSIS AND SEVERE HEPATOMEGALY WITH STEATOSIS, and EXACERBATIONS OF HEPATITIS B

Zidovudine, a component of COMBIVIR (lamivudine and zidovudine) tablets, has been associated with hematologic toxicity including neutropenia and severe anemia, particularly in patients with advanced Human Immunodeficiency Virus (HIV‑1) disease [see Warnings and Precautions (5.1)].

Prolonged use of zidovudine has been associated with symptomatic myopathy [see Warnings and Precautions (5.2)].

Lactic acidosis and severe hepatomegaly with steatosis, including fatal cases, have been reported with the use of nucleoside analogues, including lamivudine and zidovudine (components of COMBIVIR). Discontinue COMBIVIR if clinical or laboratory findings suggestive of lactic acidosis or pronounced hepatotoxicity occur [see Warnings and Precautions (5.3)].

Severe acute exacerbations of hepatitis B have been reported in patients who are co‑infected with hepatitis B virus (HBV) and HIV‑1 and have discontinued lamivudine, which is one component of COMBIVIR. Hepatic function should be monitored closely with both clinical and laboratory follow-up for at least several months in patients who discontinue COMBIVIR and are co‑infected with HIV‑1 and HBV. If appropriate, initiation of anti-hepatitis B therapy may be warranted [see Warnings and Precautions (5.4)].

1 INDICATIONS AND USAGE

COMBIVIR, a combination of 2 nucleoside analogues, is indicated in combination with other antiretrovirals for the treatment of human immunodeficiency virus type 1 (HIV‑1) infection.

2 DOSAGE AND ADMINISTRATION

2.1 Recommended Dosage for Adults and Adolescents

The recommended dosage of COMBIVIR in HIV‑1‑infected adults and adolescents weighing greater than or equal to 30 kg is 1 tablet (containing 150 mg of lamivudine and 300 mg of zidovudine) taken orally twice daily.

2.2 Recommended Dosage for Pediatric Patients

The recommended dosage of scored COMBIVIR tablets for pediatric patients who weigh greater than or equal to 30 kg and for whom a solid oral dosage form is appropriate is 1 tablet administered orally twice daily.

Before prescribing COMBIVIR tablets, children should be assessed for the ability to swallow tablets. If a child is unable to reliably swallow a COMBIVIR tablet, the liquid oral formulations should be prescribed: EPIVIR (lamivudine) oral solution and RETROVIR (zidovudine) syrup.

2.3 Not Recommended Due to Lack of Dosage Adjustment

Because COMBIVIR is a fixed‑dose tablet and cannot be dose adjusted, COMBIVIR is not recommended for:

- pediatric patients weighing less than 30 kg [see Use in Specific Populations (8.4)].
- patients with creatinine clearance less than 50 mL per minute [see Use in Specific Populations (8.6)].
- patients with hepatic impairment [see Use in Specific Populations (8.7)].
- patients experiencing dose‑limiting adverse reactions.

Liquid and solid oral formulations of the individual components of COMBIVIR are available for these populations.

3 DOSAGE FORMS AND STRENGTHS

COMBIVIR tablets contain 150 mg of lamivudine and 300 mg of zidovudine. The tablets are white, scored, film‑coated, modified capsule‑shaped tablets, debossed on both tablet faces, such that when broken in half, the full “GX FC3” code is present on both halves of the tablet (“GX” on one face and “FC3” on the opposite face of the tablet).

4 CONTRAINDICATIONS

COMBIVIR is contraindicated in patients with a previous hypersensitivity reaction to lamivudine or zidovudine.

5 WARNINGS AND PRECAUTIONS

5.1 Hematologic Toxicity/Bone Marrow Suppression

Zidovudine, a component of COMBIVIR, has been associated with hematologic toxicity including neutropenia and anemia, particularly in patients with advanced HIV‑1 disease. COMBIVIR should be used with caution in patients who have bone marrow compromise evidenced by granulocyte count less than 1,000 cells per mm^3 or hemoglobin less than 9.5 grams per dL [see Adverse Reactions (6.1)].

Frequent blood counts are strongly recommended in patients with advanced HIV‑1 disease who are treated with COMBIVIR. Periodic blood counts are recommended for other HIV‑1‑infected patients. If anemia or neutropenia develops, dosage interruption may be needed.

5.2 Myopathy

Myopathy and myositis, with pathological changes similar to that produced by HIV‑1 disease, have been associated with prolonged use of zidovudine, and therefore may occur with therapy with COMBIVIR.

5.3 Lactic Acidosis and Severe Hepatomegaly with Steatosis

Lactic acidosis and severe hepatomegaly with steatosis, including fatal cases, have been reported with the use of nucleoside analogues, including lamivudine and zidovudine (components of COMBIVIR). A majority of these cases have been in women. Female sex and obesity may be risk factors for the development of lactic acidosis and severe hepatomegaly with steatosis in patients treated with antiretroviral nucleoside analogues. See full prescribing information for EPIVIR (lamivudine) and RETROVIR (zidovudine). Treatment with COMBIVIR should be suspended in any patient who develops clinical or laboratory findings suggestive of lactic acidosis or pronounced hepatotoxicity, which may include hepatomegaly and steatosis even in the absence of marked transaminase elevations.

5.4 Patients with Hepatitis B Virus Co-infection

Posttreatment Exacerbations of Hepatitis

Clinical and laboratory evidence of exacerbations of hepatitis have occurred after discontinuation of lamivudine. See full prescribing information for EPIVIR (lamivudine). Patients should be closely monitored with both clinical and laboratory follow‑up for at least several months after stopping treatment.

Emergence of Lamivudine‑Resistant HBV

Safety and efficacy of lamivudine have not been established for treatment of chronic hepatitis B in subjects dually infected with HIV-1 and HBV. Emergence of hepatitis B virus variants associated with resistance to lamivudine has been reported in HIV–1-infected subjects who have received lamivudine‑containing antiretroviral regimens in the presence of concurrent infection with hepatitis B virus. See full prescribing information for EPIVIR (lamivudine).

5.5 Use with Interferon- and Ribavirin–Based Regimens

Patients receiving interferon alfa with or without ribavirin and COMBIVIR should be closely monitored for treatment‑associated toxicities, especially hepatic decompensation, neutropenia, and anemia. See full prescribing information for RETROVIR (zidovudine). Discontinuation of COMBIVIR should be considered as medically appropriate. Dose reduction or discontinuation of interferon alfa, ribavirin, or both should also be considered if worsening clinical toxicities are observed, including hepatic decompensation (e.g., Child-Pugh greater than 6) (see full prescribing information for interferon and ribavirin).

Exacerbation of anemia has been reported in HIV–1/HCV co–infected patients receiving ribavirin and zidovudine. Coadministration of ribavirin and COMBIVIR is not advised.

5.6 Pancreatitis

COMBIVIR should be used with caution in patients with a history of pancreatitis or other significant risk factors for the development of pancreatitis. Treatment with COMBIVIR should be stopped immediately if clinical signs, symptoms, or laboratory abnormalities suggestive of pancreatitis occur [see Adverse Reactions (6.1)].

5.7 Immune Reconstitution Syndrome

Immune reconstitution syndrome has been reported in patients treated with combination antiretroviral therapy, including COMBIVIR. During the initial phase of combination antiretroviral treatment, patients whose immune systems respond may develop an inflammatory response to indolent or residual opportunistic infections (such as Mycobacterium avium infection, cytomegalovirus, Pneumocystis jirovecii pneumonia [PCP], or tuberculosis), which may necessitate further evaluation and treatment.

Autoimmune disorders (such as Graves’ disease, polymyositis, and Guillain-Barré syndrome) have also been reported to occur in the setting of immune reconstitution; however, the time to onset is more variable, and can occur many months after initiation of treatment.

5.8 Lipoatrophy

Treatment with zidovudine, a component of COMBIVIR, has been associated with loss of subcutaneous fat. The incidence and severity of lipoatrophy are related to cumulative exposure. This fat loss, which is most evident in the face, limbs, and buttocks, may be only partially reversible and improvement may take months to years after switching to a non-zidovudine-containing regimen. Patients should be regularly assessed for signs of lipoatrophy during therapy with zidovudine-containing products, and if feasible, therapy should be switched to an alternative regimen if there is suspicion of lipoatrophy.

6 ADVERSE REACTIONS

The following adverse reactions are discussed in other sections of the labeling:

- Hematologic toxicity, including neutropenia and anemia [see Boxed Warning, Warnings and Precautions (5.1)].
- Symptomatic myopathy [see Boxed Warning, Warnings and Precautions (5.2)].
- Lactic acidosis and severe hepatomegaly with steatosis [see Boxed Warning, Warnings and Precautions (5.3)].
- Exacerbations of hepatitis B [see Boxed Warning, Warnings and Precautions (5.4)].
- Hepatic decompensation in patients co-infected with HIV‑1 and hepatitis C [see Warnings and Precautions (5.5)].
- Exacerbation of anemia in HIV‑1/HCV co-infected patients receiving ribavirin and zidovudine [see Warnings and Precautions (5.5)].
- Pancreatitis [see Warnings and Precautions (5.6)].
- Immune reconstitution syndrome [see Warnings and Precautions (5.7)].
- Lipoatrophy [see Warnings and Precautions (5.8)].

6.1 Clinical Trials Experience

Because clinical trials are conducted under widely varying conditions, adverse reaction rates observed in the clinical trials of a drug cannot be directly compared with rates in the clinical trials of another drug and may not reflect the rates observed in clinical practice.

Lamivudine plus Zidovudine Administered as Separate Formulations

In 4 randomized, controlled trials of EPIVIR 300 mg per day plus RETROVIR 600 mg per day, the following selected adverse reactions and laboratory abnormalities were observed (Tables 1 and 2).

Table 1. Selected Clinical Adverse Reactions (Greater than or Equal to 5% Frequency) in 4 Controlled Clinical Trials with EPIVIR 300 mg per Day and RETROVIR 600 mg per Day
Adverse Reaction | EPIVIR plus RETROVIR; (n = 251)
Body as a whole
Headache | 35%
Malaise & fatigue | 27%
Fever or chills | 10%
Digestive
Nausea | 33%
Diarrhea | 18%
Nausea & vomiting | 13%
Anorexia and/or decreased appetite | 10%
Abdominal pain | 9%
Abdominal cramps | 6%
Dyspepsia | 5%
Nervous system
Neuropathy | 12%
Insomnia & other sleep disorders | 11%
Dizziness | 10%
Depressive disorders | 9%
Respiratory
Nasal signs & symptoms | 20%
Cough | 18%
Skin
Skin rashes | 9%
Musculoskeletal
Musculoskeletal pain | 12%
Myalgia | 8%
Arthralgia | 5%

Pancreatitis was observed in 9 of the 2,613 adult subjects (0.3%) who received EPIVIR in controlled clinical trials [see Warnings and Precautions (5.6)].

Selected laboratory abnormalities observed during therapy are listed in Table 2.

Table 2. Frequencies of Selected Laboratory Abnormalities among Adults in 4 Controlled Clinical Trials of EPIVIR 300 mg per Day plus RETROVIR 600 mg per Daya
Test; (Abnormal Level) | EPIVIR plus RETROVIR; % (n)
Neutropenia (ANC <750/mm^3) | 7.2% (237)
Anemia (Hgb <8.0 g/dL) | 2.9% (241)
Thrombocytopenia (platelets <50,000/mm^3) | 0.4% (240)
ALT (>5.0 x ULN) | 3.7% (241)
AST (>5.0 x ULN) | 1.7% (241)
Bilirubin (>2.5 x ULN) | 0.8% (241)
Amylase (>2.0 x ULN) | 4.2% (72)
ULN = Upper limit of normal.
ANC = Absolute neutrophil count.
n = Number of subjects assessed.
a Frequencies of these laboratory abnormalities were higher in subjects with mild laboratory abnormalities at baseline.

6.2 Postmarketing Experience

The following adverse reactions have been identified during postmarketing use. Because these reactions are reported voluntarily from a population of unknown size, it is not always possible to reliably estimate their frequency or establish a causal relationship to drug exposure.

Body as a Whole

Redistribution/accumulation of body fat [see Warnings and Precautions (5.8)].

Cardiovascular

Cardiomyopathy.

Endocrine and Metabolic

Gynecomastia, hyperglycemia.

Gastrointestinal

Oral mucosal pigmentation, stomatitis.

General

Vasculitis, weakness.

Hemic and Lymphatic

Anemia, (including pure red cell aplasia and anemias progressing on therapy), lymphadenopathy, splenomegaly.

Hepatic and Pancreatic

Lactic acidosis and hepatic steatosis, pancreatitis, posttreatment exacerbations of hepatitis B [see Boxed Warning, Warnings and Precautions (5.3), (5.4), (5.6)].

Hypersensitivity

Sensitization reactions (including anaphylaxis), urticaria.

Musculoskeletal

Muscle weakness, CPK elevation, rhabdomyolysis.

Nervous

Paresthesia, peripheral neuropathy, seizures.

Respiratory

Abnormal breath sounds/wheezing.

Skin

Alopecia, erythema multiforme, Stevens‑Johnson syndrome.

7 DRUG INTERACTIONS

7.1 Zidovudine

Agents Antagonistic with Zidovudine

Concomitant use of zidovudine with the following drugs should be avoided since an antagonistic relationship has been demonstrated in vitro:

- Stavudine
- Doxorubicine
- Nucleoside analogues, e.g., ribavirin

Hematologic/Bone Marrow Suppressive/Cytotoxic Agents

Coadministration with the following drugs may increase the hematologic toxicity of zidovudine:

- Ganciclovir
- Interferon alfa
- Ribavirin
- Other bone marrow suppressive or cytotoxic agents

7.2 Lamivudine

Sorbitol

Coadministration of single doses of lamivudine and sorbitol resulted in a sorbitol dose-dependent reduction in lamivudine exposures. When possible, avoid use of sorbitol-containing medicines with lamivudine-containing medicines [see Clinical Pharmacology (12.3)].

8 USE IN SPECIFIC POPULATIONS

8.1 Pregnancy

Pregnancy Exposure Registry

There is a pregnancy exposure registry that monitors pregnancy outcomes in women exposed to COMBIVIR during pregnancy. Healthcare providers are encouraged to register patients by calling the Antiretroviral Pregnancy Registry (APR) at 1-800-258-4263.

Risk Summary

Available data from the APR show no difference in the overall risk of birth defects for lamivudine or zidovudine compared with the background rate for birth defects of 2.7% in the Metropolitan Atlanta Congenital Defects Program (MACDP) reference population (see Data). The APR uses the MACDP as the U.S. reference population for birth defects in the general population. The MACDP evaluates women and infants from a limited geographic area and does not include outcomes for births that occurred at less than 20 weeks’ gestation. The rate of miscarriage is not reported in the APR. The estimated background rate of miscarriage in clinically recognized pregnancies in the U.S. general population is 15% to 20%. The background risk for major birth defects and miscarriage for the indicated population is unknown.

Hyperlactatemia, which may be due to mitochondrial dysfunction, has been reported in infants with in utero exposure to zidovudine-containing products. These events were transient and asymptomatic in most cases. There have been few reports of developmental delay, seizures, and other neurological disease. However, a causal relationship between these events and exposure to zidovudine-containing products in utero or peri-partum has not been established (see Data).

In animal reproduction studies, oral administration of lamivudine to pregnant rabbits during organogenesis resulted in embryolethality at systemic exposure (AUC) similar to the recommended clinical dose; however, no adverse development effects were observed with oral administration of lamivudine to pregnant rats during organogenesis at plasma concentrations (Cmax) 35 times the recommended clinical dose. Administration of oral zidovudine to female rats prior to mating and throughout gestation resulted in embryotoxicity at doses that produced systemic exposure (AUC) approximately 33 times higher than exposure at the recommended clinical dose. However, no embryotoxicity was observed after oral administration of zidovudine to pregnant rats during organogenesis at doses that produced systemic exposure (AUC) approximately 117 times higher than exposures at the recommended clinical dose. Administration of oral zidovudine to pregnant rabbits during organogenesis resulted in embryotoxicity at doses that produced systemic exposure (AUC) approximately 108 times higher than exposure at the recommended clinical dose. However, no embryotoxicity was observed at doses that produced systemic exposure (AUC) approximately 23 times higher than exposures at the recommended clinical dose (see Data).

Data

Human Data: Lamivudine: Based on prospective reports to the APR of over 11,000 exposures to lamivudine during pregnancy resulting in live births (including over 4,500 exposed in the first trimester), there was no difference between the overall risk of birth defects for lamivudine compared with the background birth defect rate of 2.7% in a U.S. reference population of the MACDP. The prevalence of birth defects in live births was 3.1% (95% CI: 2.6% to 3.6%) following first trimester exposure to lamivudine-containing regimens and 2.8% (95% CI: 2.5% to 3.3%) following second/third trimester exposure to lamivudine-containing regimens.

Lamivudine pharmacokinetics were studied in pregnant women during 2 clinical trials conducted in South Africa. The trial assessed pharmacokinetics in 16 women at 36 weeks’ gestation using 150 mg lamivudine twice daily with zidovudine, 10 women at 38 weeks’ gestation using 150 mg lamivudine twice daily with zidovudine, and 10 women at 38 weeks’ gestation using lamivudine 300 mg twice daily without other antiretrovirals. These trials were not designed or powered to provide efficacy information. Lamivudine concentrations were generally similar in maternal, neonatal, and umbilical cord serum samples. In a subset of subjects, amniotic fluid specimens were collected following natural rupture of membranes and confirmed that lamivudine crosses the placenta in humans. Based on limited data at delivery, median (range) amniotic fluid concentrations of lamivudine were 3.9 (1.2 to 12.8)–fold greater compared with paired maternal serum concentration (n = 8).

Zidovudine: Based on prospective reports to the APR of over 13,000 exposures to zidovudine during pregnancy resulting in live births (including over 4,000 exposed in the first trimester), there was no difference between the overall risk of birth defects for zidovudine compared with the background birth defect rate of 2.7% in a U.S. reference population of the MACDP. The prevalence of birth defects in live births was 3.2% (95% CI: 2.7% to 3.8%) following first trimester exposure to zidovudine-containing regimens and 2.8% (95% CI: 2.5% to 3.2%) following second/third trimester exposure to zidovudine-containing regimens.

A randomized, double-blind, placebo-controlled trial was conducted in HIV–1-infected pregnant women to determine the utility of zidovudine for the prevention of maternal-fetal HIV-1 transmission. Zidovudine treatment during pregnancy reduced the rate of maternal-fetal HIV-1 transmission from 24.9% for infants born to placebo-treated mothers to 7.8% for infants born to mothers treated with zidovudine. There were no differences in pregnancy-related adverse events between the treatment groups. Of the 363 neonates that were evaluated, congenital abnormalities occurred with similar frequency between neonates born to mothers who received zidovudine and neonates born to mothers who received placebo. The observed abnormalities included problems in embryogenesis (prior to 14 weeks) or were recognized on ultrasound before or immediately after initiation of trial drug [see Clinical Studies (14.2)].

Zidovudine has been shown to cross the placenta and concentrations in neonatal plasma at birth were essentially equal to those in maternal plasma at delivery [see Clinical Pharmacology (12.3)]. There have been reports of mild, transient elevations in serum lactate levels, which may be due to mitochondrial dysfunction, in neonates and infants exposed in utero or peri-partum to zidovudine-containing products. There have been few reports of developmental delay, seizures, and other neurological disease. However, a causal relationship between these events and exposure to zidovudine-containing products in utero or peri-partum has not been established. The clinical relevance of transient elevations in serum lactate is unknown.

Animal Data: Lamivudine: Lamivudine was administered orally to pregnant rats (at 90, 600, and 4,000 mg per kg per day) and rabbits (at 90, 300, and 1,000 mg per kg per day and at 15, 40, and 90 mg per kg per day) during organogenesis (on gestation Days 7 through 16 [rat] and 8 through 20 [rabbit]). No evidence of fetal malformations due to lamivudine was observed in rats and rabbits at doses producing plasma concentrations (Cmax) approximately 35 times higher than human exposure at the recommended daily dose. Evidence of early embryolethality was seen in the rabbit at system exposures (AUC) similar to those observed in humans, but there was no indication of this effect in the rat at plasma concentrations (Cmax) 35 times higher than human exposure at the recommended daily dose. Studies in pregnant rats showed that lamivudine is transferred to the fetus through the placenta. In the fertility/pre-and postnatal development study in rats, lamivudine was administered orally at doses of 180, 900, and 4,000 mg per kg per day (from prior to mating through postnatal Day 20). In the study, development of the offspring, including fertility and reproductive performance, was not affected by maternal administration of lamivudine.

Zidovudine: A study in pregnant rats (at 50, 150, or 450 mg per kg per day starting 26 days prior to mating through gestation to postnatal Day 21) showed increased fetal resorptions at doses that produced systemic exposures (AUC) approximately 33 times higher than exposure at the recommended daily human dose (300 mg twice daily). However, in an oral embryo-fetal development study in rats (at 125, 250, or 500 mg per kg per day on gestation Days 6 through 15), no fetal resorptions were observed at doses that produced systemic exposure (AUC) approximately 117 times higher than exposures at the recommended daily human dose. An oral embryo-fetal development study in rabbits (at 75, 150, or 500 mg per kg per day on gestation Days 6 through 18) showed increased fetal resorptions at the 500 mg-per-kg-per-day dose, which produced systemic exposures (AUC) approximately 108 times higher than exposure at the recommended daily human dose; however, no fetal resorptions were noted at doses up to 150 mg per kg per day, which produced systemic exposure (AUC) approximately 23 times higher than exposures at the recommended daily human dose. These oral embryo-fetal development studies in the rat and rabbit revealed no evidence of fetal malformations with zidovudine. In another developmental toxicity study, pregnant rats (dosed at 3,000 mg per kg per day from Days 6 through 15 of gestation) showed marked maternal toxicity and an increased incidence of fetal malformations at exposures greater than 300 times the recommended daily human dose based on AUC. However, there were no signs of fetal malformations at doses up to 600 mg per kg per day.

8.2 Lactation

Risk Summary

The Centers for Disease Control and Prevention recommends that HIV‑1-infected mothers in the United States not breastfeed their infants to avoid risking postnatal transmission of HIV‑1 infection. Lamivudine and zidovudine are present in human milk. There is no information on the effects of lamivudine or zidovudine on the breastfed infant or the effects of the drugs on milk production. Because of the potential for (1) HIV‑1 transmission (in HIV-negative infants), (2) developing viral resistance (in HIV-positive infants), and (3) adverse reactions in a breastfed infant similar to those seen in adults, instruct mothers not to breastfeed if they are receiving COMBIVIR.

8.4 Pediatric Use

COMBIVIR is not recommended for use in pediatric patients who weigh less than 30 kg because it is a fixed‑dose combination tablet that cannot be adjusted for this patient population [see Dosage and Administration (2.2)].

8.5 Geriatric Use

Clinical trials of COMBIVIR did not include sufficient numbers of subjects aged 65 and over to determine whether they respond differently from younger subjects. In general, caution should be exercised in the administration of COMBIVIR in elderly patients reflecting the greater frequency of decreased hepatic, renal, or cardiac function, and of concomitant disease or other drug therapy [see Clinical Pharmacology (12.3)].

8.6 Patients with Impaired Renal Function

COMBIVIR is not recommended for patients with creatinine clearance less than 50 mL per min because COMBIVIR is a fixed‑dose combination and the dosage of the individual components cannot be adjusted. If a dose reduction of the lamivudine or zidovudine components of COMBIVIR is required for patients with renal impairment then the individual components should be used [see Dosage and Administration (2.3), Clinical Pharmacology (12.3)].

8.7 Patients with Impaired Hepatic Function

COMBIVIR is a fixed‑dose combination and the dosage of the individual components cannot be adjusted. Zidovudine is primarily eliminated by hepatic metabolism and zidovudine concentrations are increased in patients with impaired hepatic function, which may increase the risk of hematologic toxicity. Frequent monitoring of hematologic toxicities is advised.

10 OVERDOSAGE

There is no known specific treatment for overdose with COMBIVIR. If overdose occurs, the patient should be monitored and standard supportive treatment applied as required.

Lamivudine

Because a negligible amount of lamivudine was removed via (4‑hour) hemodialysis, continuous ambulatory peritoneal dialysis, and automated peritoneal dialysis, it is not known if continuous hemodialysis would provide clinical benefit in a lamivudine overdose event.

Zidovudine

Acute overdoses of zidovudine have been reported in pediatric patients and adults. These involved exposures up to 50 grams. No specific symptoms or signs have been identified following acute overdosage with zidovudine apart from those listed as adverse events such as fatigue, headache, vomiting, and occasional reports of hematological disturbances. Patients recovered without permanent sequelae. Hemodialysis and peritoneal dialysis appear to have a negligible effect on the removal of zidovudine, while elimination of its primary metabolite, 3′-azido-3′-deoxy-5′-O-β-D-glucopyranuronosylthymidine (GZDV), is enhanced.

11 DESCRIPTION

COMBIVIR tablets are combination tablets containing lamivudine and zidovudine. Lamivudine (EPIVIR) and zidovudine (RETROVIR, azidothymidine, AZT, or ZDV) are synthetic nucleoside analogues with activity against HIV‑1.

COMBIVIR tablets are for oral administration. Each film‑coated tablet contains 150 mg of lamivudine, 300 mg of zidovudine, and the inactive ingredients colloidal silicon dioxide, hypromellose, magnesium stearate, microcrystalline cellulose, polyethylene glycol, polysorbate 80, sodium starch glycolate, and titanium dioxide.

Lamivudine

The chemical name of lamivudine is (2R,cis)-4-amino-1-(2-hydroxymethyl-1,3-oxathiolan-5-yl)-(1H)-pyrimidin-2-one. Lamivudine is the (‑)enantiomer of a dideoxy analogue of cytidine. Lamivudine has also been referred to as (‑)2′,3′-dideoxy, 3′-thiacytidine. It has a molecular formula of C8H11N3O3S and a molecular weight of 229.3 g per mol. It has the following structural formula:

Lamivudine is a white to off‑white crystalline solid and is soluble in water.

Zidovudine

The chemical name of zidovudine is 3′-azido-3′-deoxythymidine. It has a molecular formula of C10H13N5O4 and a molecular weight of 267.24 g per mol. It has the following structural formula:

Zidovudine is a white to beige, odorless, crystalline solid with a solubility of 20.1 mg per mL in water at 25°C.

12 CLINICAL PHARMACOLOGY

12.1 Mechanism of Action

COMBIVIR is an antiretroviral agent [see Microbiology (12.4)].

12.3 Pharmacokinetics

Pharmacokinetics in Adults

One COMBIVIR tablet was bioequivalent to 1 EPIVIR tablet (150 mg) plus 1 RETROVIR tablet (300 mg) following single‑dose administration to fasting healthy subjects (n = 24).

Lamivudine: Following oral administration, lamivudine is rapidly absorbed and extensively distributed. Binding to plasma protein is low. Approximately 70% of an intravenous dose of lamivudine is recovered as unchanged drug in the urine. Metabolism of lamivudine is a minor route of elimination (approximately 5% of an oral dose after 12 hours). In humans, the only known metabolite is the trans‑sulfoxide metabolite (approximately 5% of an oral dose after 12 hours).

Zidovudine: Following oral administration, zidovudine is rapidly absorbed and extensively distributed. Binding to plasma protein is low. Zidovudine is eliminated primarily by hepatic metabolism. The major metabolite of zidovudine is GZDV. GZDV area under the curve (AUC) is about 3‑fold greater than the zidovudine AUC. Urinary recovery of zidovudine and GZDV accounts for 14% and 74% of the dose following oral administration, respectively. A second metabolite, 3′-amino-3′-deoxythymidine (AMT), has been identified in plasma. The AMT AUC was one-fifth of the zidovudine AUC.

In humans, lamivudine and zidovudine are not significantly metabolized by cytochrome P450 enzymes.

The pharmacokinetic properties of lamivudine and zidovudine in fasting subjects are summarized in Table 3.

Table 3. Pharmacokinetic Parametersa for Lamivudine and Zidovudine in Adults
Parameter | Lamivudine |  | Zidovudine
Oral bioavailability (%) | 86 ± 16 | n = 12 | 64 ± 10 | n = 5
Apparent volume of distribution (L/kg) | 1.3 ± 0.4 | n = 20 | 1.6 ± 0.6 | n = 8
Plasma protein binding (%) | <36 |  | <38
CSF:plasma ratiob | 0.12 [0.04 to 0.47] | n = 38c | 0.60 [0.04 to 2.62] | n = 39d
Systemic clearance (L/h/kg) | 0.33 ± 0.06 | n = 20 | 1.6 ± 0.6 | n = 6
Renal clearance (L/h/kg) | 0.22 ± 0.06 | n = 20 | 0.34 ± 0.05 | n = 9
Elimination half-life (h)e | 5 to 7 |  | 0.5 to 3
a Data presented as mean ± standard deviation except where noted.
b Median [range].
c Children.
d Adults.
e Approximate range.

Effect of Food on Absorption of COMBIVIR: COMBIVIR may be administered with or without food. The lamivudine and zidovudine AUC following administration of COMBIVIR with food was similar when compared with fasting healthy subjects (n = 24).

Specific Populations

Patients with Renal Impairment: COMBIVIR: The effect of renal impairment on the combination of lamivudine and zidovudine has not been evaluated (see the U.S. prescribing information for the individual lamivudine and zidovudine components).

Patients with Hepatic Impairment: COMBIVIR: The effect of hepatic impairment on the combination of lamivudine, and zidovudine has not been evaluated (see the U.S. prescribing information for the individual lamivudine and zidovudine components).

Pregnant Women: Lamivudine: Lamivudine pharmacokinetics were studied in 36 pregnant women during 2 clinical trials conducted in South Africa. Lamivudine pharmacokinetics in pregnant women were similar to those seen in non-pregnant adults and in postpartum women. Lamivudine concentrations were generally similar in maternal, neonatal, and umbilical cord serum samples.

Zidovudine: Zidovudine pharmacokinetics have been studied in a Phase 1 trial of 8 women during the last trimester of pregnancy. Zidovudine pharmacokinetics were similar to those of non-pregnant adults. Consistent with passive transmission of the drug across the placenta, zidovudine concentrations in neonatal plasma at birth were essentially equal to those in maternal plasma at delivery.

Although data are limited, methadone maintenance therapy in 5 pregnant women did not appear to alter zidovudine pharmacokinetics.

Geriatric Patients: The pharmacokinetics of lamivudine and zidovudine have not been studied in subjects over 65 years of age.

Male and Female Patients: There are no significant or clinically relevant gender differences in the pharmacokinetics of the individual components (lamivudine or zidovudine) based on the available information that was analyzed for each of the individual components.

Racial Groups: Lamivudine: There are no significant or clinically relevant racial differences in lamivudine pharmacokinetics based on the available information that was analyzed for the individual lamivudine component.

Zidovudine: The pharmacokinetics of zidovudine with respect to race have not been determined.

Drug Interaction Studies

No drug interaction trials have been conducted using COMBIVIR tablets.

Lamivudine and Zidovudine: No clinically significant alterations in lamivudine or zidovudine pharmacokinetics were observed in 12 asymptomatic HIV‑1-infected adult subjects given a single dose of zidovudine (200 mg) in combination with multiple doses of lamivudine (300 mg every 12 hours).

Interferon Alfa: There was no significant pharmacokinetic interaction between lamivudine and interferon alfa in a trial of 19 healthy male subjects.

Ribavirin: In vitro data indicate ribavirin reduces phosphorylation of lamivudine, stavudine, and zidovudine. However, no pharmacokinetic (e.g., plasma concentrations or intracellular triphosphorylated active metabolite concentrations) or pharmacodynamic (e.g., loss of HIV‑1/HCV virologic suppression) interaction was observed when ribavirin and lamivudine (n = 18), stavudine (n = 10), or zidovudine (n = 6) were coadministered as part of a multi-drug regimen to HIV‑1/HCV co‑infected subjects.

Sorbitol (Excipient): Lamivudine and sorbitol solutions were coadministered to 16 healthy adult subjects in an open-label, randomized-sequence, 4-period, crossover trial. Each subject received a single 300-mg dose of lamivudine oral solution alone or coadministered with a single dose of 3.2 grams, 10.2 grams, or 13.4 grams of sorbitol in solution. Coadministration of lamivudine with sorbitol resulted in dose-dependent decreases of 20%, 39%, and 44% in the AUC(0-24); 14%, 32%, and 36% in the AUC(∞); and 28%, 52%, and 55% in the Cmax: of lamivudine, respectively.

Table 4 presents drug interaction information for the individual components of COMBIVIR.

Table 4. Effect of Coadministered Drugs on Lamivudine and Zidovudine AUCa
Coadministered Drug and Dose | Drug and Dose | n | Concentrations of Lamivudine or Zidovudine |  | Concentration of Coadministered Drug
Coadministered Drug and Dose | Drug and Dose | n | AUC | Variability | Concentration of Coadministered Drug
Nelfinavir; 750 mg every 8 h x 7 to 10 days | Lamivudine; single 150 mg | 11 | ↑10% | 95% CI:; 1% to 20% | ↔
Trimethoprim 160 mg/; Sulfamethoxazole 800 mg daily x 5 days | Lamivudine; single 300 mg | 14 | ↑43% | 90% CI:; 32% to 55% | ↔
Atovaquone; 750 mg every 12 h; with food | Zidovudine; 200 mg every 8 h | 14 | ↑31% | Range:; 23% to 78%b | ↔
Clarithromycin; 500 mg twice daily | Zidovudine 100 mg every 4 h x 7 days | 4 | ↓12% | Range:; ↓34% to ↑14% | Not Reported
Fluconazole; 400 mg daily | Zidovudine 200 mg every 8 h | 12 | ↑74% | 95% CI:; 54% to 98% | Not Reported
Methadone; 30 to 90 mg daily | Zidovudine 200 mg every 4 h | 9 | ↑43% | Range:; 16% to 64%b | ↔
Nelfinavir; 750 mg every 8 h x 7 to 10 days | Zidovudine single 200 mg | 11 | ↓35% | Range:; 28% to 41% | ↔
Probenecid; 500 mg every 6 h x 2 days | Zidovudine 2 mg/kg every 8 h x 3 days | 3 | ↑106% | Range:; 100% to 170%b | Not Assessed
Rifampin; 600 mg daily x; 14 days | Zidovudine 200 mg every 8 h x 14 days | 8 | ↓47% | 90% CI:; 41% to 53% | Not Assessed
Ritonavir; 300 mg every 6 h x 4 days | Zidovudine 200 mg every 8 h x 4 days | 9 | ↓25% | 95% CI:; 15% to 34% | ↔
Valproic acid; 250 mg or 500 mg every 8 h x 4 days | Zidovudine 100 mg every 8 h x 4 days | 6 | ↑80% | Range:; 64% to 130%b | Not Assessed
↑ = Increase; ↓= Decrease; ↔ = No significant change; AUC = Area under the concentration versus time curve; CI = Confidence interval.
a This table is not all inclusive.
b Estimated range of percent difference.

12.4 Microbiology

Mechanism of Action

Lamivudine: Lamivudine is a synthetic nucleoside analogue. Intracellularly, lamivudine is phosphorylated to its active 5′-triphosphate metabolite, lamivudine triphosphate (3TC‑TP). The principal mode of action of 3TC‑TP is inhibition of reverse transcriptase (RT) via DNA chain termination after incorporation of the nucleotide analogue.

Zidovudine: Zidovudine is a synthetic nucleoside analogue. Intracellularly, zidovudine is phosphorylated to its active 5′-triphosphate metabolite, zidovudine triphosphate (ZDV‑TP). The principal mode of action of ZDV‑TP is inhibition of RT via DNA chain termination after incorporation of the nucleotide analogue.

Antiviral Activity

Lamivudine plus Zidovudine: In HIV‑1-infected MT‑4 cells, lamivudine in combination with zidovudine at various ratios was not antagonistic.

Lamivudine: The antiviral activity of lamivudine against HIV‑1 was assessed in a number of cell lines including monocytes and fresh human peripheral blood lymphocytes (PBMCs) using standard susceptibility assays. EC50 values were in the range of 0.003 to 15 microM (1 microM = 0.23 mcg per mL). The median EC50 values of lamivudine were 60 nM (range: 20 to 70 nM), 35 nM (range: 30 to 40 nM), 30 nM (range: 20 to 90 nM), 20 nM (range: 3 to 40 nM), 30 nM (range: 1 to 60 nM), 30 nM (range: 20 to 70 nM), 30 nM (range: 3 to 70 nM), and 30 nM (range: 20 to 90 nM) against HIV‑1 clades A-G and group O viruses (n = 3 except n = 2 for clade B) respectively. The EC50 values against HIV‑2 isolates (n = 4) ranged from 0.003 to 0.120 microM in PBMCs. Ribavirin (50 microM) used in the treatment of chronic HCV infection decreased the anti-HIV‑1 activity of lamivudine by 3.5‑fold in MT‑4 cells.

Zidovudine: The antiviral activity of zidovudine against HIV‑1 was assessed in a number of cell lines including monocytes and fresh human peripheral blood lymphocytes. The EC50 and EC90 values for zidovudine were 0.01 to 0.49 microM (1 microM = 0.27 mcg per mL) and 0.1 to 9 microM, respectively. HIV‑1 from therapy‑naive subjects with no amino acid substitutions associated with resistance gave median EC50 values of 0.011 microM (range: 0.005 to 0.110 microM) from Virco (n = 92 baseline samples) and 0.0017 microM (range: 0.006 to 0.0340 microM) from Monogram Biosciences (n = 135 baseline samples). The EC50 values of zidovudine against different HIV‑1 clades (A-G) ranged from 0.00018 to 0.02 microM, and against HIV‑2 isolates from 0.00049 to 0.004 microM. Ribavirin has been found to inhibit the phosphorylation of zidovudine in cell culture.

Neither lamivudine nor zidovudine was antagonistic to tested anti-HIV agents, with the exception of stavudine where an antagonistic relationship with zidovudine has been demonstrated in cell culture. See full prescribing information for EPIVIR (lamivudine) and RETROVIR (zidovudine).

Resistance

In subjects receiving lamivudine monotherapy or combination therapy with lamivudine plus zidovudine, HIV‑1 isolates from most subjects became phenotypically and genotypically resistant to lamivudine within 12 weeks.

HIV‑1 strains resistant to both lamivudine and zidovudine have been isolated from subjects after prolonged lamivudine/zidovudine therapy. Dual resistance required the presence of multiple amino acid substitutions, the most essential of which may be G333E. The incidence of dual resistance and the duration of combination therapy required before dual resistance occurs are unknown.

Lamivudine: Lamivudine‑resistant isolates of HIV‑1 have been selected in cell culture and have also been recovered from subjects treated with lamivudine or lamivudine plus zidovudine. Genotypic analysis of isolates selected in cell culture and recovered from lamivudine‑treated subjects showed that the resistance was due to a specific amino acid substitution in the HIV‑1 reverse transcriptase at codon 184 changing the methionine to either valine or isoleucine (M184V/I).

Zidovudine: HIV‑1 isolates with reduced susceptibility to zidovudine have been selected in cell culture and were also recovered from subjects treated with zidovudine. Genotypic analyses of the isolates selected in cell culture and recovered from zidovudine‑treated subjects showed thymidine analogue mutation (TAM) substitutions in HIV‑1 RT (M41L, D67N, K70R, L210W, T215Y or F, and K219E/R/H/Q/N) that confer zidovudine resistance. In general, higher levels of resistance were associated with greater number of substitutions.

In some subjects harboring zidovudine‑resistant virus at baseline, phenotypic sensitivity to zidovudine was restored by 12 weeks of treatment with lamivudine and zidovudine.

Cross‑Resistance

Cross‑resistance has been observed among NRTIs. Cross‑resistance between lamivudine and zidovudine has not been reported. In some subjects treated with lamivudine alone or in combination with zidovudine, isolates have emerged with a substitution at codon 184, which confers resistance to lamivudine.

TAM substitutions are selected by zidovudine and confer cross‑resistance to abacavir, didanosine, stavudine, and tenofovir.

13 NONCLINICAL TOXICOLOGY

13.1 Carcinogenesis, Mutagenesis, Impairment of Fertility

Carcinogenicity

Lamivudine: Long‑term carcinogenicity studies with lamivudine in mice and rats showed no evidence of carcinogenic potential at exposures up to 10 times (mice) and 58 times (rats) the human exposures at the recommended dose of 300 mg.

Zidovudine: Zidovudine was administered orally at 3 dosage levels to separate groups of mice and rats (60 females and 60 males in each group). Initial single daily doses were 30, 60, and 120 mg per kg per day in mice and 80, 220, and 600 mg per kg per day in rats. The doses in mice were reduced to 20, 30, and 40 mg per kg per day after Day 90 because of treatment‑related anemia, whereas in rats only the high dose was reduced to 450 mg per kg per day on Day 91 and then to 300 mg per kg per day on Day 279.

In mice, 7 late‑appearing (after 19 months) vaginal neoplasms (5 non-metastasizing squamous cell carcinomas, 1 squamous cell papilloma, and 1 squamous polyp) occurred in animals given the highest dose. One late‑appearing squamous cell papilloma occurred in the vagina of a middle-dose animal. No vaginal tumors were found at the lowest dose.

In rats, 2 late‑appearing (after 20 months), non-metastasizing vaginal squamous cell carcinomas occurred in animals given the highest dose. No vaginal tumors occurred at the low or middle dose in rats. No other drug‑related tumors were observed in either sex of either species.

At doses that produced tumors in mice and rats, the estimated drug exposure (as measured by AUC) was approximately 3 times (mouse) and 24 times (rat) the estimated human exposure at the recommended therapeutic dose of 100 mg every 4 hours.

It is not known how predictive the results of rodent carcinogenicity studies may be for humans.

Mutagenicity

Lamivudine: Lamivudine was mutagenic in an L5178Y mouse lymphoma assay and clastogenic in a cytogenetic assay using cultured human lymphocytes. Lamivudine was not mutagenic in a microbial mutagenicity assay, in an in vitro cell transformation assay, in a rat micronucleus test, in a rat bone marrow cytogenetic assay, and in an assay for unscheduled DNA synthesis in rat liver.

Zidovudine: Zidovudine was mutagenic in an L5178Y mouse lymphoma assay, positive in an in vitro cell transformation assay, clastogenic in a cytogenetic assay using cultured human lymphocytes, and positive in mouse and rat micronucleus tests after repeated doses. It was negative in a cytogenetic study in rats given a single dose.

Impairment of Fertility

Lamivudine: Lamivudine did not affect male or female fertility in rats at doses up to 4,000 mg per kg per day, associated with concentrations approximately 42 times (male) or 63 times (female) higher than the concentrations (Cmax) in humans at the dose of 300 mg.

Zidovudine: Zidovudine, administered to male and female rats at doses up to 450 mg per kg per day, which is 7 times the recommended adult dose (300 mg twice daily) based on body surface area, had no effect on fertility based on conception rates.

14 CLINICAL STUDIES

One COMBIVIR tablet given twice daily is an alternative regimen to EPIVIR tablets 150 mg twice daily plus RETROVIR 600 mg per day in divided doses.

14.1 Adults

The NUCB3007 (CAESAR) trial was conducted using EPIVIR 150‑mg tablets (150 mg twice daily) and RETROVIR 100‑mg capsules (2 x 100 mg 3 times daily). CAESAR was a multi‑center, double-blind, placebo-controlled trial comparing continued current therapy (zidovudine alone [62% of subjects] or zidovudine with didanosine or zalcitabine [38% of subjects]) to the addition of EPIVIR or EPIVIR plus an investigational non-nucleoside reverse transcriptase inhibitor, randomized 1:2:1. A total of 1,816 HIV‑1-infected adults with 25 to 250 (median 122) CD4 cells per mm^3 at baseline were enrolled: median age was 36 years, 87% were male, 84% were nucleoside-experienced, and 16% were therapy‑naive. The median duration on trial was 12 months. Results are summarized in Table 5.

Table 5. Number of Subjects (%) with at Least 1 HIV-1 Disease-Progression Event or Death
Endpoint | Current Therapy (n = 460) | EPIVIR; plus Current Therapy; (n = 896) | EPIVIR; plus a NNRTIa; plus Current Therapy (n = 460)
HIV‑1 progression or death | 90 (19.6%) | 86 (9.6%) | 41 (8.9%)
Death | 27 (5.9%) | 23 (2.6%) | 14 (3.0%)
a An investigational non-nucleoside reverse transcriptase inhibitor not approved in the United States.

14.2 Prevention of Maternal-Fetal HIV-1 Transmission

The utility of zidovudine alone for the prevention of maternal-fetal HIV‑1 transmission was demonstrated in a randomized, double-blind, placebo-controlled trial conducted in HIV‑1‑infected pregnant women with CD4+ cell counts of 200 to 1,818 cells per mm^3 (median in the treated group: 560 cells per mm^3) who had little or no previous exposure to zidovudine. Oral zidovudine was initiated between 14 and 34 weeks of gestation (median 11 weeks of therapy) followed by IV administration of zidovudine during labor and delivery. Following birth, neonates received oral zidovudine syrup for 6 weeks. The trial showed a statistically significant difference in the incidence of HIV‑1 infection in the neonates (based on viral culture from peripheral blood) between the group receiving zidovudine and the group receiving placebo. Of 363 neonates evaluated in the trial, the estimated risk of HIV‑1 infection was 7.8% in the group receiving zidovudine and 24.9% in the placebo group, a relative reduction in transmission risk of 68.7%. Zidovudine was well tolerated by mothers and infants. There was no difference in pregnancy-related adverse events between the treatment groups.

16 HOW SUPPLIED/STORAGE AND HANDLING

COMBIVIR tablets, containing 150 mg lamivudine and 300 mg zidovudine, are white, scored, film‑coated, modified‑capsule-shaped tablets, debossed on both tablet faces, such that when broken in half, the full “GXFC3” code is present on both halves of the tablet (“GX” on one face and “FC3” on the opposite face of the tablet). They are available as follows:

60 Tablets/Bottle (NDC 49702-202-18).

Store between 2° and 30°C (36° and 86°F).

17 PATIENT COUNSELING INFORMATION

Neutropenia and Anemia

Inform patients that the important toxicities associated with zidovudine are neutropenia and/or anemia. Inform them of the extreme importance of having their blood counts followed closely while on therapy, especially for patients with advanced HIV‑1 disease [see Boxed Warning, Warnings and Precautions (5.1)].

Myopathy

Inform patients that myopathy and myositis with pathological changes, similar to that produced by HIV‑1 disease, have been associated with prolonged use of zidovudine [see Warnings and Precautions (5.2)].

Lactic Acidosis/Hepatomegaly with Steatosis

Advise patients that lactic acidosis and severe hepatomegaly with steatosis have been reported with use of nucleoside analogues and other antiretrovirals. Advise patients to stop taking COMBIVIR if they develop clinical symptoms suggestive of lactic acidosis or pronounced hepatotoxicity [see Warnings and Precautions (5.3)].

Patients with Hepatitis B or C Co-infection

Advise patients co‑infected with HIV‑1 and HBV that worsening of liver disease has occurred in some cases when treatment with lamivudine was discontinued. Advise patients to discuss any changes in regimen with their healthcare provider [see Warnings and Precautions (5.4)].

Inform patients with HIV‑1/HCV co-infection that hepatic decompensation (some fatal) has occurred in HIV‑1/HCV co-infected patients receiving combination antiretroviral therapy for HIV‑1 and interferon alfa with or without ribavirin [see Warnings and Precautions (5.5)].

Drug Interactions

Advise patients that other medications may interact with COMBIVIR and certain medications, including ganciclovir, interferon alfa, and ribavirin, may exacerbate the toxicity of zidovudine, a component of COMBIVIR [see Drug Interactions (7.1)].

Immune Reconstitution Syndrome

Advise patients to inform their healthcare provider immediately of any signs and symptoms of infection as inflammation from previous infection may occur soon after combination antiretroviral therapy, including when COMBIVIR is started [see Warnings and Precautions (5.7)].

Lipoatrophy

Advise patients that loss of subcutaneous fat may occur in patients receiving COMBIVIR and that they will be regularly assessed during therapy [see Warnings and Precautions (5.8)].

Pregnancy Registry

Advise patients that there is a pregnancy exposure registry that monitors pregnancy outcomes in women exposed to COMBIVIR during pregnancy [see Use in Specific Populations (8.1)].

Lactation

Instruct women with HIV-1 infection not to breastfeed because HIV-1 can be passed to the baby in the breast milk [see Use in Specific Populations (8.2)].

Missed Dose

Instruct patients that if they miss a dose of COMBIVIR, to take it as soon as they remember. Advise patients not to double their next dose or take more than the prescribed dose [see Dosage and Administration (2)].

Trademarks are owned by or licensed to the ViiV Healthcare group of companies.

Manufactured for:

ViiV Healthcare
Durham, NC 27701

©2023 ViiV Healthcare group of companies or its licensor.

CMB:11PI

PACKAGE LABEL

PRINCIPAL DISPLAY PANEL

NDC 49702-202-18

COMBIVIR

(lamivudine and zidovudine)

Tablets 150 mg/300 mg

Rx only

60 Tablets

Each tablet contains 150 mg of lamivudine and 300 mg of zidovudine.

Store between 2o and 30oC (36o and 86oF).

See prescribing information for dosage information.

Do not use if printed safety seal under cap is broken or missing.

Manufactured for:

ViiV Healthcare

Research Triangle Park, NC 27709

by:

GlaxoSmithKline

Research Triangle Park, NC 27709

Trademarks are owned or licensed by ViiV Healthcare.

©2018 ViiV Healthcare or licensor.

Made in UK

10000000149610 Rev. 9/18